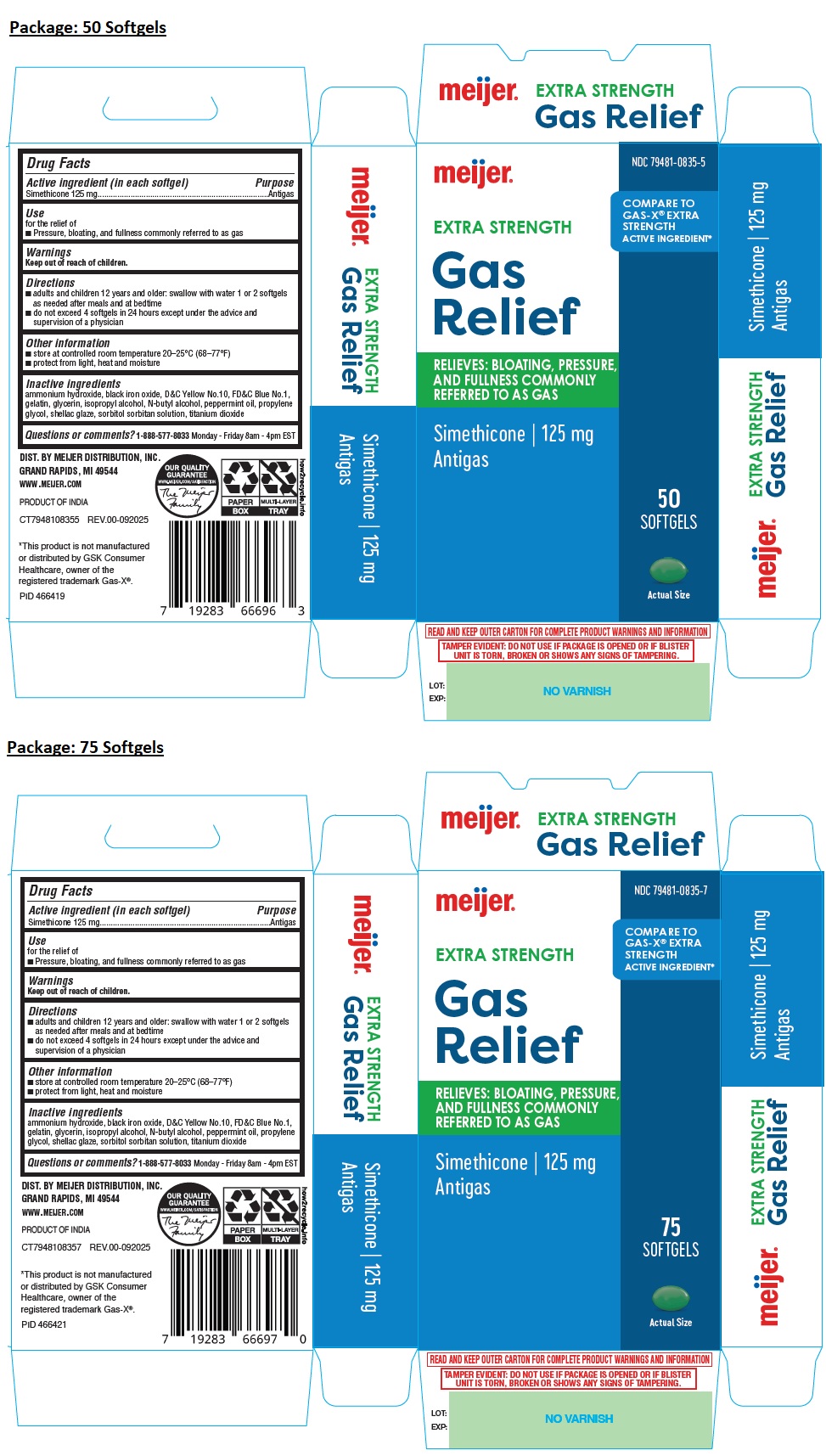 DRUG LABEL: meijer EXTRA STRENGTH Gas Relief
NDC: 79481-0835 | Form: CAPSULE, LIQUID FILLED
Manufacturer: Meijer, Inc
Category: otc | Type: HUMAN OTC DRUG LABEL
Date: 20251029

ACTIVE INGREDIENTS: DIMETHICONE, UNSPECIFIED 125 mg/1 1
INACTIVE INGREDIENTS: AMMONIA; FERROSOFERRIC OXIDE; D&C YELLOW NO. 10; FD&C BLUE NO. 1; GELATIN, UNSPECIFIED; GLYCERIN; ISOPROPYL ALCOHOL; BUTYL ALCOHOL; PEPPERMINT OIL; PROPYLENE GLYCOL; SHELLAC; SORBITOL; SORBITAN; TITANIUM DIOXIDE

meijer® EXTRA STRENGTH Gas Relief

Active ingredient (in each softgel)

Simethicone 125 mg

Purpose

Antigas

Use

for the relief of
• Pressure, bloating, and fullness commonly referred to as gas

Warnings

Keep out of reach of children.

Directions

• adults and children 12 years and older: swallow with water 1 or 2 softgels as needed after meals and at bedtime
• do not exceed 4 softgels in 24 hours except under the advice and supervision of a physician

Other information

• store at controlled room temperature 20–25°C (68–77°F)
• protect from light, heat and moisture

Inactive ingredients

ammonium hydroxide, black iron oxide, D&C Yellow No.10, FD&C Blue No.1, gelatin, glycerin, isopropyl alcohol, N-butyl alcohol, peppermint oil, propylene glycol, shellac glaze, sorbitol sorbitan solution, titanium dioxide

Questions or comments?

1-888-577-8033 Monday - Friday 8am - 4pm EST

RELIEVES: BLOATING, PRESSURE, AND FULLNESS COMMONLY REFERRED TO AS GAS

COMPARE TO GAS-X® EXTRA STRENGTH ACTIVE INGREDIENT*

DIST. BY MEIJER DISTRIBUTION, INC. GRAND RAPIDS, MI 49544

WWW.MEIJER.COM

PRODUCT OF INDIA

*This product is not manufactured or distributed by GSK Consumer Healthcare, owner of the registered trademark Gas-X®.

READ AND KEEP OUTER CARTON FOR COMPLETE PRODUCT WARNINGS AND INFORMATION

TAMPER EVIDENT: DO NOT USE IF PACKAGE IS OPENED OR IF BLISTER UNIT IS TORN, BROKEN OR SHOWS ANY SIGNS OF TAMPERING.